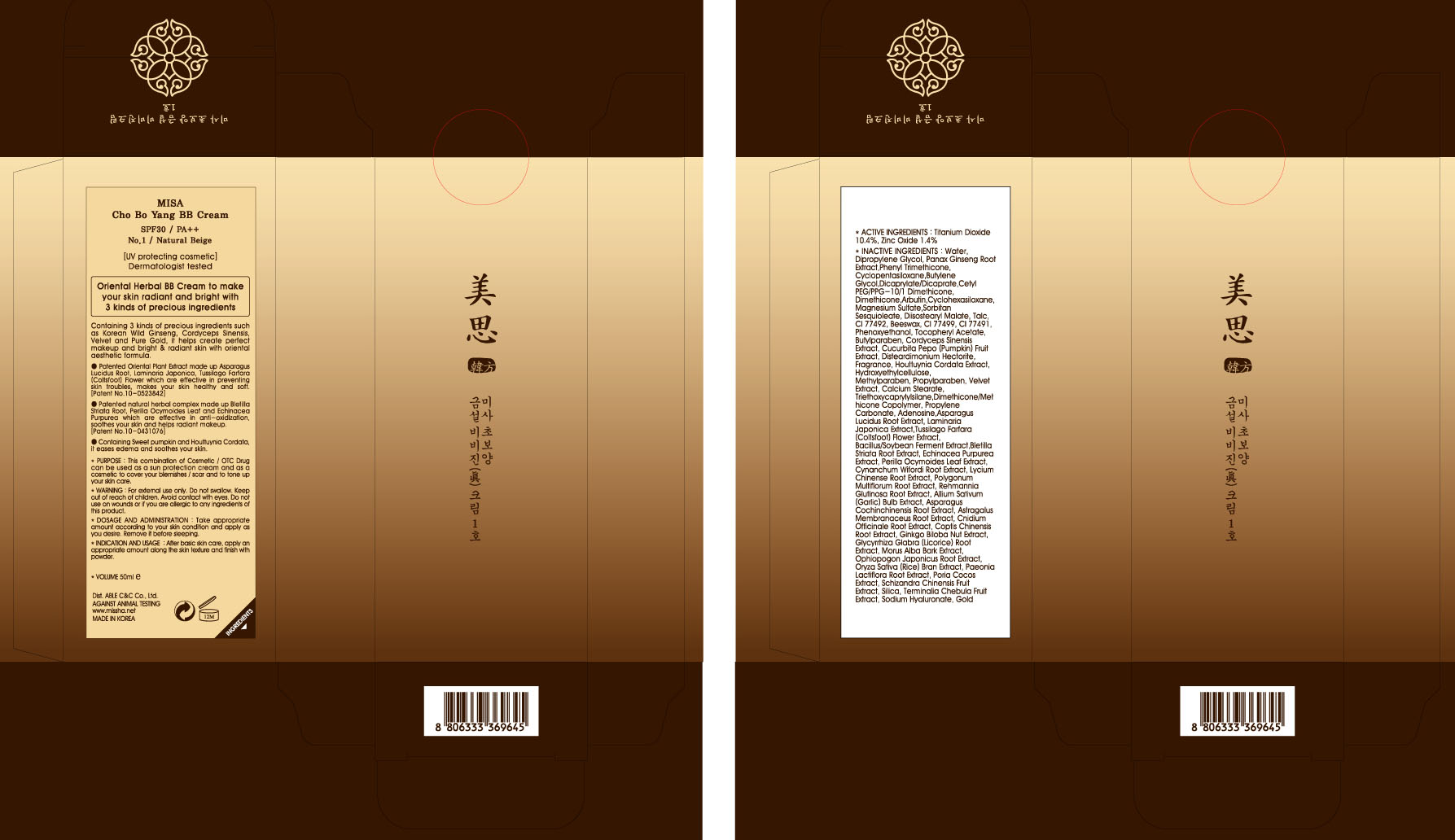 DRUG LABEL: MISA CHO BO YANG BB
NDC: 13733-011 | Form: CREAM
Manufacturer: ABLE C&C CO., LTD.
Category: otc | Type: HUMAN OTC DRUG LABEL
Date: 20111120

ACTIVE INGREDIENTS: TITANIUM DIOXIDE 5.2 mL/50 mL; ZINC OXIDE 0.7 mL/50 mL
INACTIVE INGREDIENTS: WATER; DIPROPYLENE GLYCOL; ASIAN GINSENG; PHENYL TRIMETHICONE; CYCLOMETHICONE 5; DIMETHICONE; ARBUTIN; CYCLOMETHICONE 6; MAGNESIUM SULFATE, UNSPECIFIED; SORBITAN SESQUIOLEATE; TALC; YELLOW WAX; PHENOXYETHANOL; BUTYLPARABEN; OPHIOCORDYCEPS SINENSIS; PUMPKIN; HOUTTUYNIA CORDATA FLOWERING TOP; METHYLPARABEN; PROPYLPARABEN; CALCIUM STEARATE; TRIETHOXYCAPRYLYLSILANE; PROPYLENE CARBONATE; ADENOSINE; ASPARAGUS COCHINCHINENSIS TUBER; LAMINARIA JAPONICA; TUSSILAGO FARFARA FLOWER; BLETILLA STRIATA BULB; ECHINACEA PURPUREA; PERILLA FRUTESCENS LEAF; LYCIUM CHINENSE ROOT BARK; FALLOPIA MULTIFLORA ROOT; REHMANNIA GLUTINOSA ROOT

Drug Facts

ACTIVE INGREDIENT

ACTIVE INGREDIENTS: Titanium Dioxide 10.4%, Zinc Oxide 1.4%

INACTIVE INGREDIENT

INACTIVE INGREDIENTS: Water, Dipropylene Glycol, Panax Ginseng Root Extract,Phenyl Trimethicone, Cyclopentasiloxane,Butylene Glycol,Dicaprylate/Dicaprate,Cetyl PEG/PPG-10/1 Dimethicone, Dimethicone,Arbutin,Cyclohexasiloxane, Magnesium Sulfate,Sorbitan Sesquioleate, Diisostearyl Malate, Talc, CI 77492, Beeswax, CI 77499, CI 77491, Phenoxyethanol, Tocopheryl Acetate, Butylparaben, Cordyceps Sinensis Extract, Cucurbita Pepo (Pumpkin) Fruit Extract, Disteardimonium Hectorite, Fragrance, Houttuynia Cordata Extract, Hydroxyethylcellulose,
Methylparaben, Propylparaben, Velvet Extract, Calcium Stearate, Triethoxycaprylylsilane,Dimethicone/Methicone Copolymer, Propylene Carbonate, Adenosine,Asparagus Lucidus Root Extract, Laminaria Japonica Extract,Tussilago Farfara (Coltsfoot) Flower Extract, Bacillus/Soybean Ferment Extract,Bletilla Striata Root Extract, Echinacea Purpurea Extract, Perilla Ocymoides Leaf Extract, Cynanchum Wifordi Root Extract, Lycium Chinense Root Extract, Polygonum Multiflorum Root Extract, Rehmannia Glutinosa Root Extract, Allium Sativum (Garlic) Bulb Extract, Asparagus Cochinchinensis Root Extract, Astragalus Membranaceus Root Extract, Cnidium Officinale Root Extract, Coptis Chinensis Root Extract, Ginkgo Biloba Nut Extract, Glycyrrhiza Glabra (Licorice) Root Extract, Morus Alba Bark Extract, Ophiopogon Japonicus Root Extract, Oryza Sativa (Rice) Bran Extract, Paeonia Lactiflora Root Extract, Poria Cocos Extract, Schizandra Chinensis Fruit Extract, Silica, Terminalia Chebula Fruit Extract, Sodium Hyaluronate, Gold

PURPOSE:
This combination of Cosmetic / OTC Drug can be used as a sun protection cream and as a cosmetic to cover your blemishes / scar and to tone up your skin care.

WARNINGS:
For external use only.
Do not swallow.
Avoid contact with eyes.
Do not use on wounds or if you are allergic to any ingredients of this product.

Keep out of reach of children:
Keep out of reach of children.

INDICATION AND USAGE:
After basic skin care, apply an appropriate amount along the skin texture and finish with powder.

DOSAGE AND ADMINISTRATION:
Take appropriate amount according to your skin condition and apply as you desire.
Remove it before sleeping.